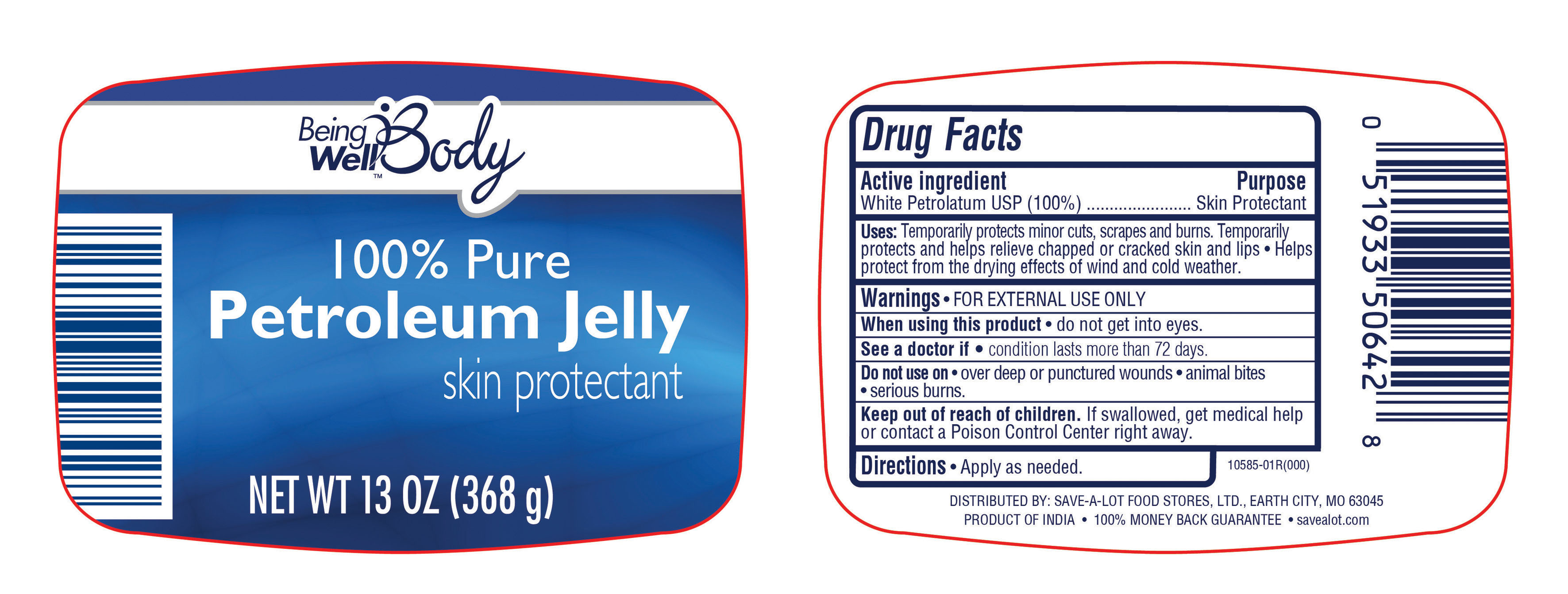 DRUG LABEL: Being Well Body
NDC: 46994-505 | Form: OINTMENT
Manufacturer: Save-A-Lot Food Stores Ltd
Category: otc | Type: HUMAN OTC DRUG LABEL
Date: 20130218

ACTIVE INGREDIENTS: PETROLATUM 1 g/1 g

Active Ingredient
White Petrolatum USP (100%)

Purpose
Skin protectant

INDICATIONS AND USAGE

Uses: Temporarily protects minor cuts, scrapes and burns. Temporarily protects and helps relieve chapped or sracked skin and lips ●Helps protect from the drying effects of wind and cold weather.

Warnings: For External Use Only

When using this product ●do not get into eyes

ASK DOCTOR

See a doctor if ●condition lasts for more than 72 hours

Do not use on ●over deep or puncture wounds ●animal bites ●serious burns

Keep out of reach of children. If swallowed, get medical help or contact a Poison Control Center right away.

DOSAGE AND ADMINISTRATION

DirectionsApply as needed